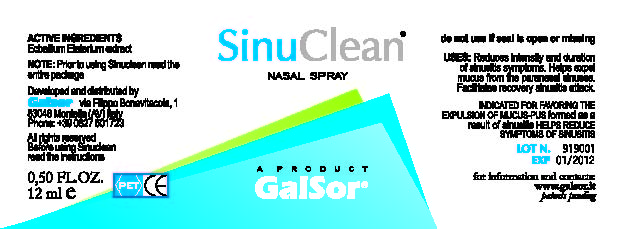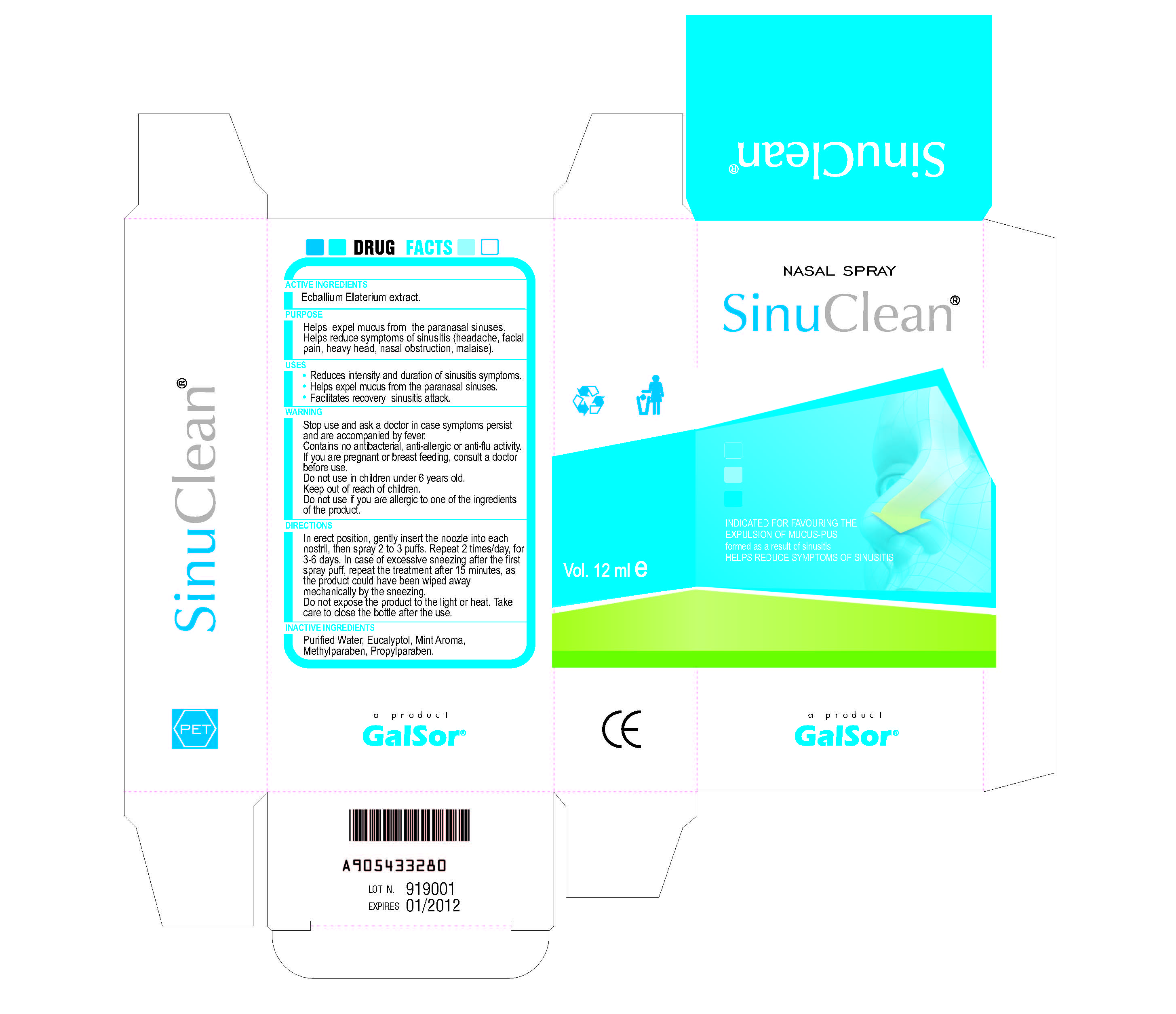 DRUG LABEL: SinuClean
NDC: 47784-001 | Form: SPRAY
Manufacturer: Galsor S.r.l
Category: homeopathic | Type: HUMAN OTC DRUG LABEL
Date: 20091022

ACTIVE INGREDIENTS: ECBALLIUM ELATERIUM FRUIT 22.09 mL/100 mL
INACTIVE INGREDIENTS: WATER; EUCALYPTOL; METHYLPARABEN; PROPYLPARABEN

ACTIVE INGREDIENT

Ecballium Elaterium extract

PURPOSE

Helps expel mucus from the paranasal sinuses.

Helps reduce symptoms of sinusitis (headache, facial pain, heavy head, nasal obstruction, malaise).

USES

- Reduces intensity and duration of sinusitis symptoms.
- Helps expel mucus from the paranasal sinuses.
- Facilitates recovery sinusitis attack.

WARNING

Stop use and ask a doctor in case symptoms persist and are accompanied by fever.

Contains no antibacterial, anti-allergic or anti-flu activity.

If you are pregnant or breast-feeding, consult a doctor before use.

Do not use in children under 6 years old.

Keep out of reach of children.

Do not use if you are allergic to one of the ingredients or the product.

DIRECTIONS

In erect position, gently insert the nozzle into each nostril, the spray 2 to 3 puffs. Repeat 2 times/day, for 3-6 days. In case of excessive sneezing after the first spray puff, repeat the treatment after 15 minutes, as the product could have been wiped away mechanically by the sneezing.,

Do not expose the product to the light or heat. Take care to close the bottle after the use.

INACTIVE INGREDIENT

Purified Water, Eucalyptol, Mint Aroma, Methylparaben, Propylparaben

PACKAGE LABEL

This section contains images of the bottle and carton labels.

This is the bottle label.

This is the carton label.